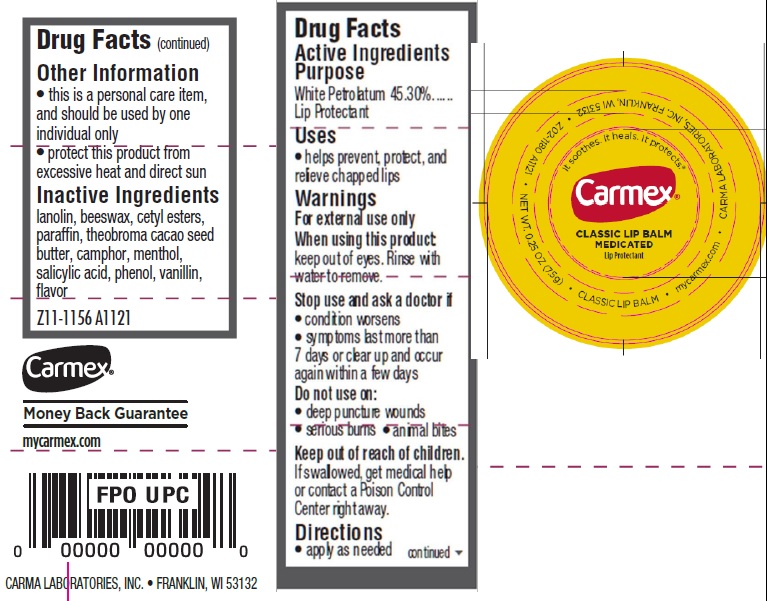 DRUG LABEL: Carmex Classic Lip Balm Medicated Lip Protectant
NDC: 10210-0055 | Form: SALVE
Manufacturer: Carma Laboratories, Inc.
Category: otc | Type: HUMAN OTC DRUG LABEL
Date: 20231106

ACTIVE INGREDIENTS: WHITE PETROLATUM 453 mg/1 g
INACTIVE INGREDIENTS: LANOLIN; YELLOW WAX; CETYL ESTERS WAX; PARAFFIN; COCOA BUTTER; CAMPHOR (SYNTHETIC); MENTHOL; SALICYLIC ACID; PHENOL; VANILLIN

Carmex Classic Lip Balm Medicated Lip Protectant

Active Ingredients

White Petrolatum 41.25%

Purpose

Lip Protectant

Uses

- helps prevent, protect, and relieve chapped lips

Warnings

For external use only

When using this product:

keep out of eyes. Rinse with water to remove.

Stop use and ask a doctor if:

- condition worsens
- symptoms last more than 7 days or clear up and occur again within a few days

Do not use

- deep puncture wounds
- serious burns
- animal bites

Keep out of reach of children.

If swallowed, get medical help or contact a Poison Control Center right away.

Directions

- apply as needed

Other Information

- this is a personal care item, and should be used by one individual only
- protect this product from excessive heat and direct sun

Inactive Ingredients

lanolin, beeswax, cetyl esters, paraffin, theobroma cacao seed butter, camphor, menthol, salicylic acid, phenol, vanillin, flavor